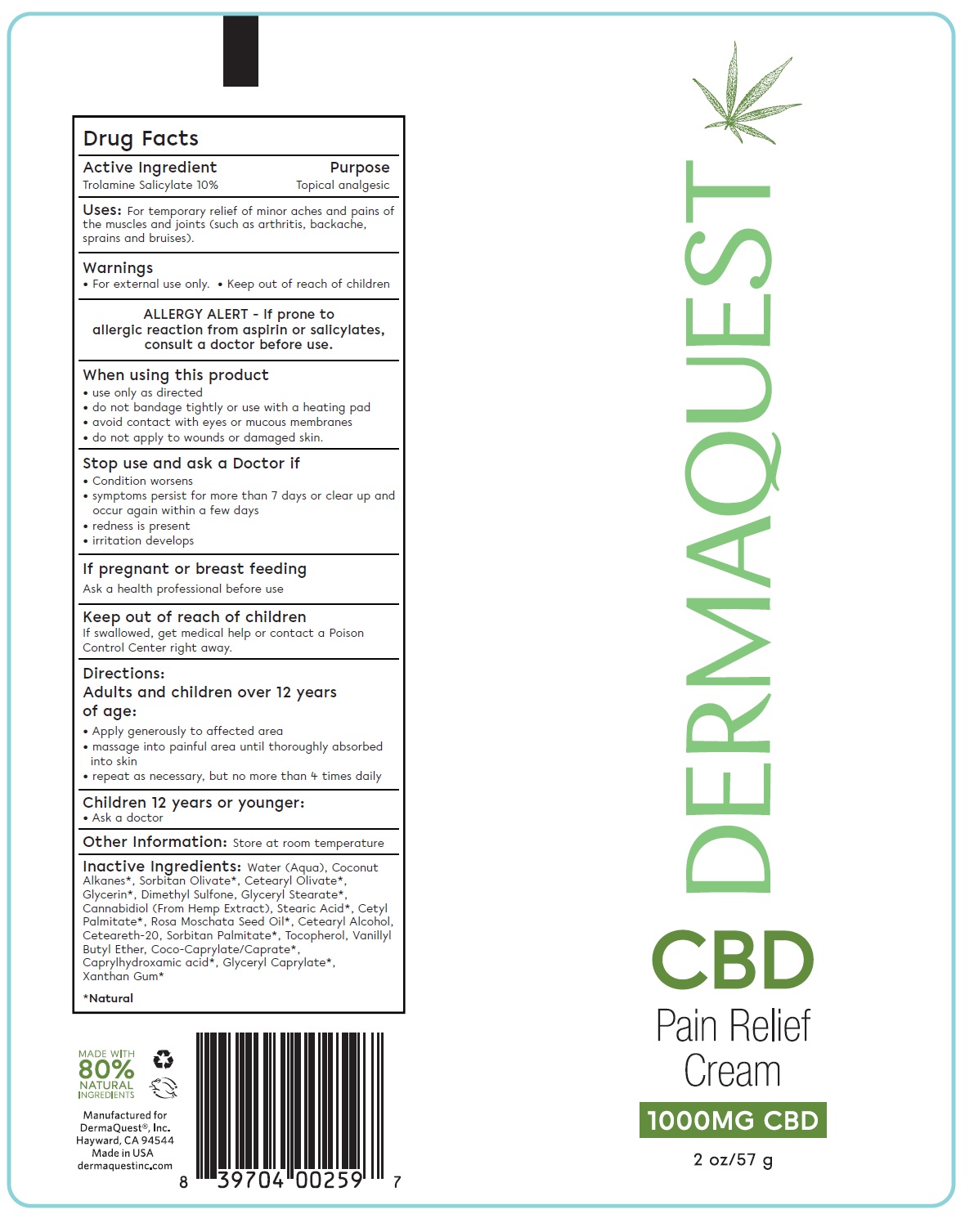 DRUG LABEL: CBD Pain Relief Cream
NDC: 62742-4198 | Form: CREAM
Manufacturer: Allure Labs
Category: otc | Type: HUMAN OTC DRUG LABEL
Date: 20241205

ACTIVE INGREDIENTS: TROLAMINE SALICYLATE 100 mg/1 g
INACTIVE INGREDIENTS: CAPRYLHYDROXAMIC ACID; COCONUT ALKANES; CANNABIDIOL; ROSA MOSCHATA SEED OIL; VANILLYL BUTYL ETHER; TOCOPHEROL; WATER; GLYCERYL MONOSTEARATE; COCO-CAPRYLATE/CAPRATE; GLYCERYL CAPRYLATE; SORBITAN OLIVATE; GLYCERIN; DIMETHYL SULFONE; SORBITAN MONOPALMITATE; CETEARYL OLIVATE; CETOSTEARYL ALCOHOL; POLYOXYL 20 CETOSTEARYL ETHER; XANTHAN GUM; CETYL PALMITATE; STEARIC ACID

Drug Facts

Active Ingredients:

Trolamine Salicylate 10%

Purpose:

Topical Analgesic

INDICATIONS AND USAGE

Uses: For temporary relief of minor aches and pains of the muscles and joints (such as arthritis, backache, sprains and bruises).

Warnings:

- For external use only
- Keep out of reach of children

When using this product

- use only as directed
- do not bandage tightly or use with a heating pad
- avoid contact eith eyes or mucus membranes
- do not apply to wounds or damaged skin

Stop use and ask a doctor if:

- Condition worsens
- symptoms persists for more tham 7 days or clear up and occurs again within few days.
- Redness is present
- irritaiotn develops

If pregnant or breat feeding

Ask a health professional before use

Keep out of reach of children

If swallowed, get medical help or contact a Poison Control Center right away.

Directions:

Adults and children over 12 years of age:
• Apply generously to affected area
• massage into painful area until thoroughly absorbed into skin
• repeat as necessary, but no more than 4 times daily

ASK DOCTOR

Children 12 years or younger:
• Ask a doctor

Other Information
• Store at room temperature

ALLERGY ALERT - If prone to allergic reaction from aspirin orsalicylates, consult a doctor before use.

INACTIVE INGREDIENT

Inactive Ingredients: Water (Aqua), Coconut Alkanes*, Sorbitan Olivate*, Cetearyl Olivate*, Glycerin*, Dimethyl Sulfone, Glyceryl Stearate*,Cannabidiol (From Hemp Extract), Stearic Acid*, Cetyl Palmitate*, Rosa Moschata Seed Oil*, Cetearyl Alcohol, Ceteareth-20, Sorbitan Palmitate*, Tocopherol, Vanillyl Butyl Ether, Coco-Caprylate/Caprate*, Caprylhydroxamic acid*, Glyceryl Caprylate*, Xanthan Gum*

PACKAGE LABEL

Manufactured for

DermaQuest®, Inc.

Hayward CA-94544

Made In USA

dermaquestinc.com